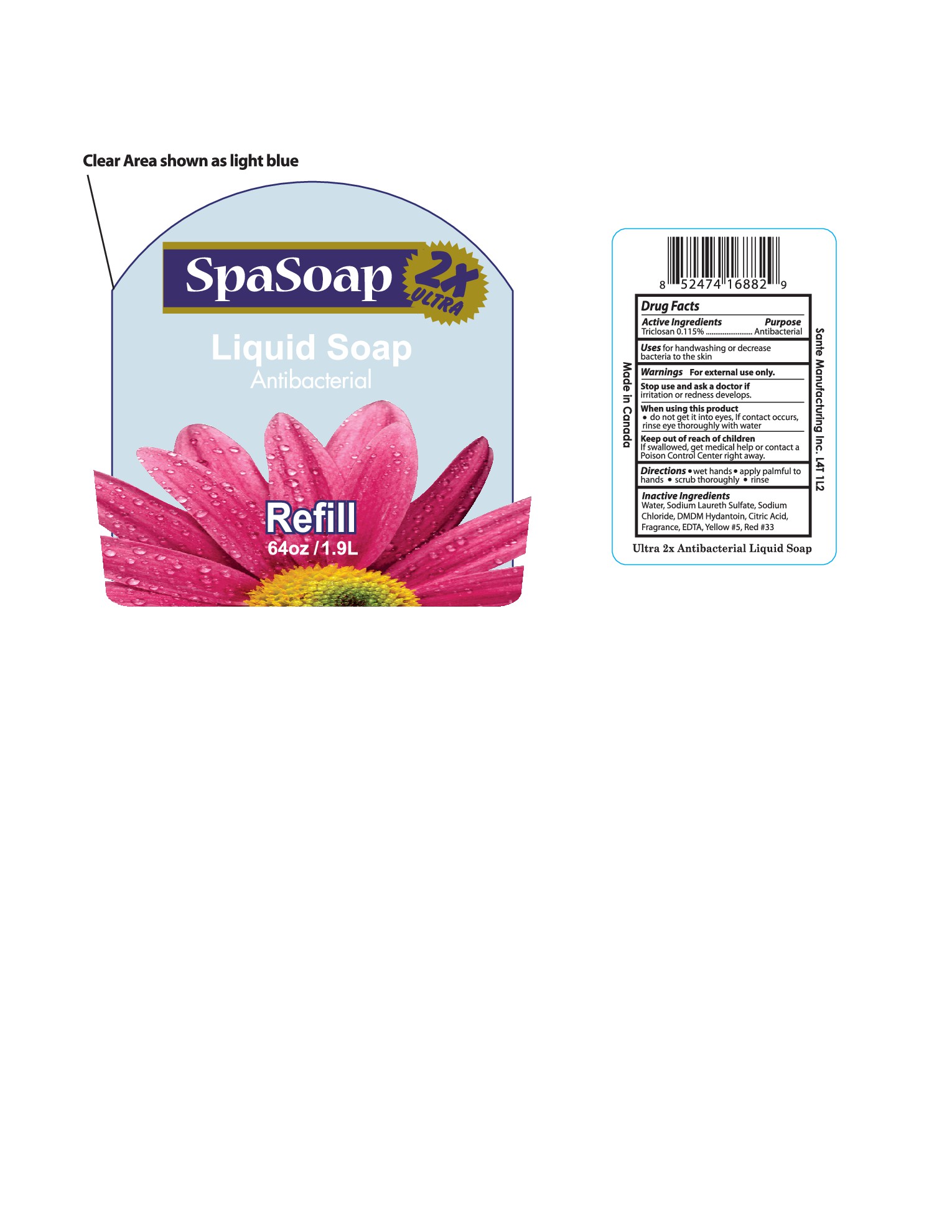 DRUG LABEL: Antibacterial
NDC: 71020-009 | Form: LIQUID
Manufacturer: Sante Manufacturing Inc
Category: otc | Type: HUMAN OTC DRUG LABEL
Date: 20161020

ACTIVE INGREDIENTS: TRICLOSAN 1.15 mg/1 mL
INACTIVE INGREDIENTS: WATER; SODIUM LAURETH SULFATE; SODIUM CHLORIDE; DMDM HYDANTOIN; EDETIC ACID; ANHYDROUS CITRIC ACID; FD&C YELLOW NO. 5; D&C RED NO. 33

Active Ingredient - Triclosan 0.115%

Purpose - Antibacterial

INDICATIONS AND USAGE

Uses - for handwashing to decrease bacteria on the skin

WARNINGS

Warning For external use only

Stop use and ask a doctor if irritation or redness develops

When using this product do not get into eyes. If contact occurs, rinse eye thoroughly with water

Keep out of reach of children. If swallowed, get medical help or contact a Poison Control Center right away

Directions

- Wet hands
- apply palmful to hands
- scrub thoroughly
- rinse

INACTIVE INGREDIENT

Water, Sodium Laureth Sulfate, Sodium Chloride, DMDM Hydantoin, Citric Acid, Fragrance, EDTA, Yellow # 5, Red# 33